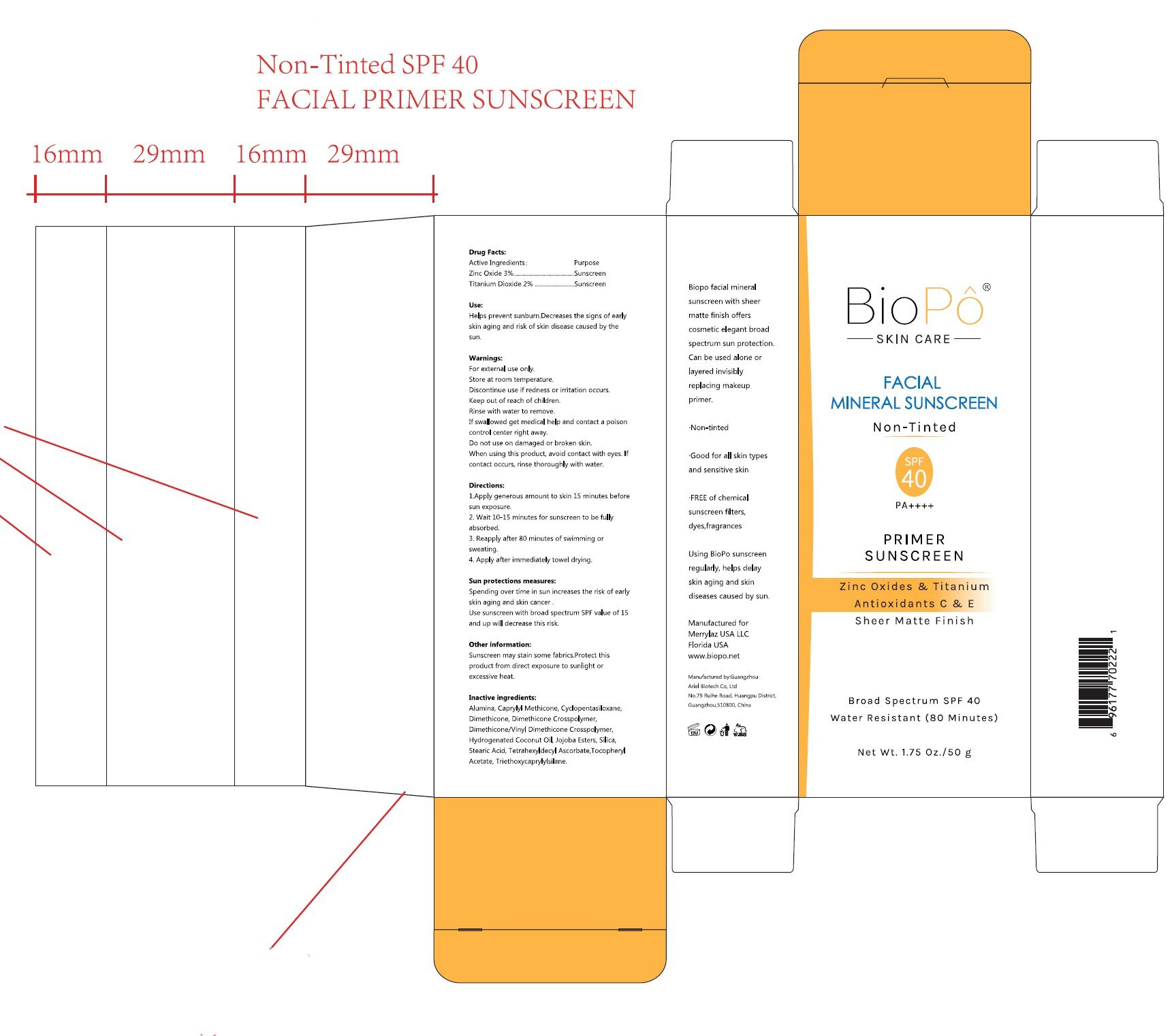 DRUG LABEL: Biopo Facial Mineral Sunscreen-Non Tinted SPF 40
NDC: 84148-014 | Form: CREAM
Manufacturer: Guangzhou Ariel Biotech Co., Ltd.
Category: otc | Type: HUMAN OTC DRUG LABEL
Date: 20251103

ACTIVE INGREDIENTS: ZINC OXIDE 3 g/100 g; TITANIUM DIOXIDE 2 g/100 g
INACTIVE INGREDIENTS: CYCLOPENTASILOXANE; DIMETHICONE; DIMETHICONE CROSSPOLYMER; DIMETHICONE/VINYL DIMETHICONE CROSSPOLYMER (HARD PARTICLE); HYDROGENATED COCONUT OIL; HYDROLYZED JOJOBA ESTERS; CAPRYLYL METHICONE; ALUMINUM HYDROXIDE; TRIETHOXYCAPRYLYLSILANE; TETRAHEXYLDECYL ASCORBATE; STEARIC ACID; SILICA; .ALPHA.-TOCOPHEROL ACETATE

84148-014

Active Ingredient(s)

Zinc Oxide 3%
Titanium Dioxide 2%

Purpose

Sunscreen

Use

Helps prevent sunburn.Decreases the signs of early
skin aging and risk of skin disease caused by the
sun.

Warnings

For external use only.
Store at room temperature.
Discontinue use if redness or irritation occurs.
Keep out of reach of children.
Rinse with water to remove.
If swallowed get medical help and contact a poison
control center right away.
Do not use on damaged or broken skin.
When using this product, avoid contact with eyes. If
contact occurs, rinse thoroughly with water.

Do not use on damaged or broken skin.

When using this product, avoid contact with eyes. If
contact occurs, rinse thoroughly with water.

Discontinue use if redness or irritation occurs.

Keep out of reach of children.

Directions

1.Apply generous amount to skin 15 minutes before sun exposure.
2. Wait 10-15 minutes for sunscreen to be fully absorbed.
3. Reapply after 80 minutes of swimming or sweating.
4. Apply after immediately towel drying.

Other information

Sunscreen may stain some fabrics.Protect this
product from direct exposure to sunlight or
excessive heat.

Inactive ingredients

Alumine, Capny Mticone, Ccoentaloxane,
Dimethicone, Dimthicone Crosolymer,"
Diethicneneinyl Dmethicone Cosolmer
Hyrogenated Coconut oi, Jjioba Esters, Sliea
Stearc Acid, Ttateyded Acoraeraa Tcohev
Acetate, Trthoxyapryilane.